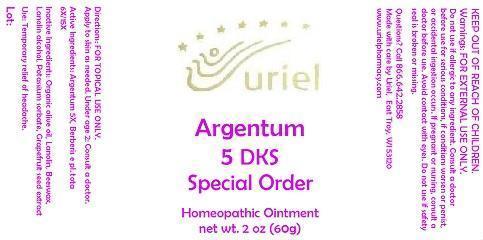 DRUG LABEL: Argentum 5 DKS Special Order
NDC: 48951-1269 | Form: OINTMENT
Manufacturer: Uriel Pharmacy Inc.
Category: homeopathic | Type: HUMAN OTC DRUG LABEL
Date: 20150220

ACTIVE INGREDIENTS: SILVER 5 [hp_X]/1 g; BERBERIS VULGARIS ROOT BARK 6 [hp_X]/1 g
INACTIVE INGREDIENTS: OLIVE OIL; LANOLIN; YELLOW WAX; LANOLIN ALCOHOLS; POTASSIUM SORBATE; CITRUS PARADISI SEED

Argentum 5 DKS Special Order

INDICATIONS AND USAGE

Directions: FOR TOPICAL USE ONLY.

DOSAGE AND ADMINISTRATION

Apply to skin as needed. Under age 2: Consult a doctor.

ACTIVE INGREDIENT

Active Ingredients: Argentum 5X, Berberis e pl. tota 6X/15X

INACTIVE INGREDIENT

Inactive Ingredients: Organic olive oil, Lanolin, Beeswax, Lanolin alcohol, Potassium sorbate, Grapefruit seed extract

PURPOSE

Use: Temporary relief of headache.

KEEP OUT OF REACH OF CHILDREN.

WARNINGS

Warnings: FOR EXTERNAL USE ONLY. Do not use if allergic to any ingredient. Consult a doctor before use for serious conditions, if conditions worsen or persist, or accidental ingestion occurs. If pregnant or nursing, consult a doctor before use. Avoid contact with eyes. Do not use if safety seal is broken or missing.

QUESTIONS

Questions? Call 866.642.2858 Made with care by Uriel, East Troy, WI 53120 www.urielpharmacy.com